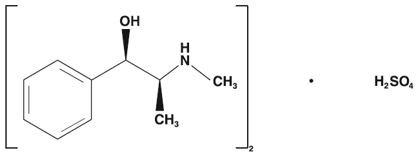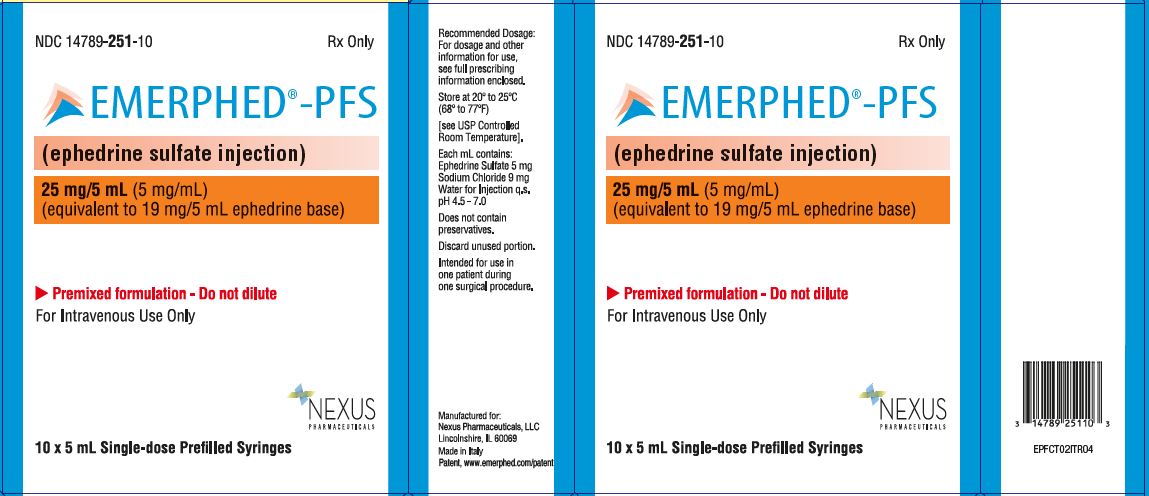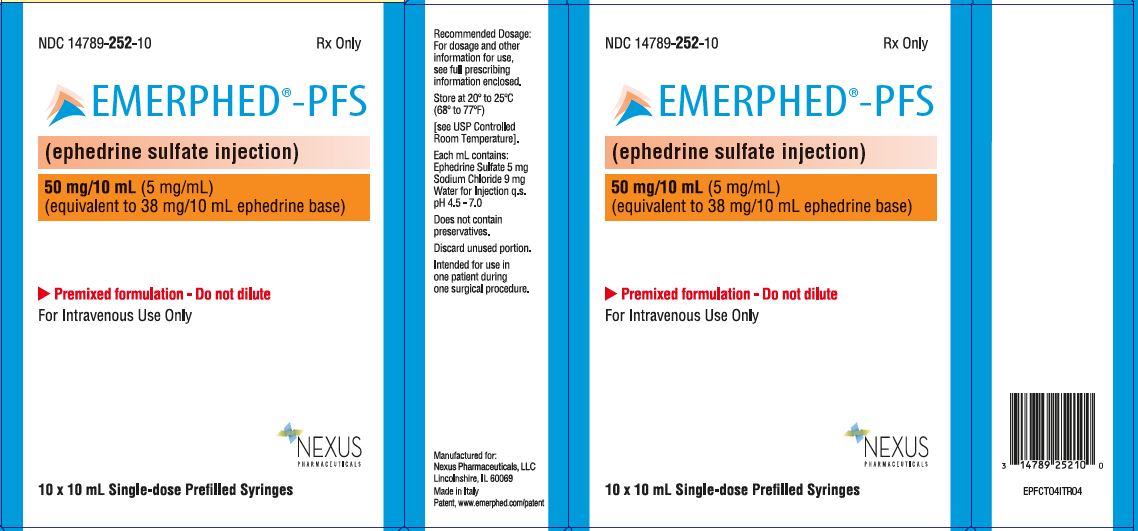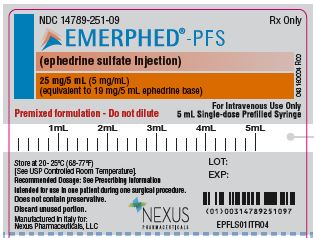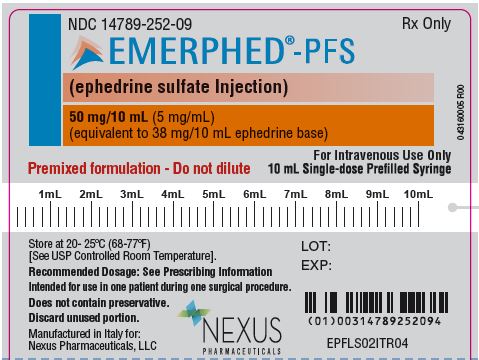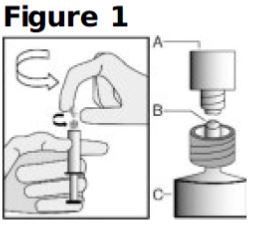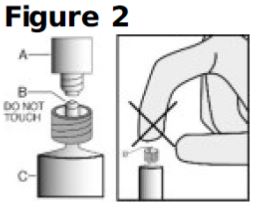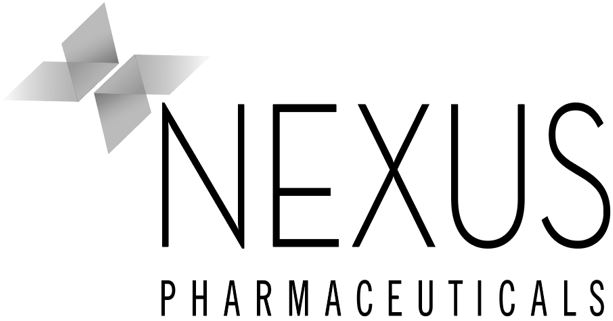 DRUG LABEL: Emerphed
NDC: 14789-252 | Form: INJECTION
Manufacturer: Nexus Pharmaceuticals, LLC
Category: prescription | Type: HUMAN PRESCRIPTION DRUG LABEL
Date: 20240916

ACTIVE INGREDIENTS: Ephedrine Sulfate 5 mg/1 mL
INACTIVE INGREDIENTS: Sodium Chloride; Water

HIGHLIGHTS OF PRESCRIBING INFORMATION

These highlights do not include all the information needed to use EMERPHED and EMERPHED-PFS safely and effectively. See full prescribing information for EMERPHED and EMERPHED-PFS.
EMERPHED® (ephedrine sulfate) injection, for intravenous use.
EMERPHED®-PFS (ephedrine sulfate injection), for intravenous use.
Initial U.S. Approval: 2016

1. INDICATIONS AND USAGE

EMERPHED and EMERPHED-PFS is an alpha- and beta- adrenergic agonist and a norepinephrine-releasing agent that is indicated for the treatment of clinically important hypotension occurring in the setting of anesthesia. (1)

2. DOSAGE AND ADMINISTRATION

- This is a premixed formulation. Do not dilute prior to use.
- Discard any unused portion of EMERPHED or EMERPHED-PFS.
- Inspect parenteral drug products visually for particulate matter and discoloration prior to administration, whenever solution and container permit.
- EMERPHED and EMERPHED-PFS is a clear, colorless solution. Do not use if the solution is not clear or if particulate matter is present.
- The single-dose prefilled syringe is intended for use in one patient during one surgical procedure.

3. DOSAGE FORMS AND STRENGTHS

Injection: 50 mg/10 mL ephedrine sulfate, equivalent to 38 mg/10 mL ephedrine base in a single-dose vial (5 mg/ mL ephedrine sulfate, equivalent to 3.8 mg/mL ephedrine base); a 25 mg/5 mL (5 mg/mL) ephedrine sulfate in a 5 mL single-dose prefilled syringe; and a 50 mg/10 mL (5 mg/mL) ephedrine sulfate in a 10 mL single-dose prefilled syringe. (3)

4. CONTRAINDICATIONS

None (4)

5. WARNINGS AND PRECAUTIONS

- Pressor Effects with Concomitant Use with Oxytocic Drugs: Pressor effect of sympathomimetic pressor amines is potentiated (5.1)
- Tachyphylaxis and Tolerance: Repeated administration of EMERPHED and EMERPHED-PFS may cause tachyphylaxis (5.2)

6. ADVERSE REACTIONS

Most common adverse reactions during treatment : nausea, vomiting, and tachycardia. (6)

To report SUSPECTED ADVERSE REACTIONS, contact Nexus Pharmaceuticals at (855) 642-2594 or FDA at 1-800-FDA-1088 or www.fda.gov/medwatch.

7. DRUG INTERACTIONS

- Interactions that Augment Pressor Effect: clonidine, oxytocin and oxytocic drugs, propofol, monoamine oxidase inhibitors (MAOIs), and atropine. Monitor blood pressure. (7)
- Interactions that Antagonize the Pressor Effect: Antagonistic effects with α-adrenergic antagonists, β-adrenergic antagonists, reserpine, quinidine, mephentermine. Monitor blood pressure. (7)
- Guanethidine: EMERPHED and EMERPHED-PFS may inhibit the neuron blockage produced by guanethidine, resulting in loss of antihypertensive effectiveness. Monitor blood pressure and adjust the dosage of pressor accordingly.
- Rocuronium: EMERPHED and EMERPHED-PFS may reduce the onset time of neuromuscular blockade when used for intubation with rocuronium if administered simultaneously with anesthetic induction. Be aware of this potential interaction. No treatment or other interventions are needed.
- Epidural anesthesia: EMERPHED and EMERPHED-PFS may decrease the efficacy of epidural blockade by hastening the regression of sensory analgesia. Monitor and treat the patient according to clinical practice.
- Theophylline: Concomitant use of EMERPHED and EMERPHED-PFS may increase the frequency of nausea, nervousness, and insomnia. Monitor patient for worsening symptoms and manage symptoms according to clinical practice.
- Cardiac glycosides: Giving EMERPHED and EMERPHED-PFS with a cardiac glycoside, such as digitalis, may increase the possibility of arrhythmias. Carefully monitor patients on cardiac glycosides who are also administered EMERPHED and EMERPHED-PFS.

FULL PRESCRIBING INFORMATION

1. INDICATIONS AND USAGE

EMERPHED and EMERPHED-PFS is indicated for the treatment of clinically important hypotension occurring in the setting of anesthesia.

2. DOSAGE AND ADMINISTRATION

2.1 General Dosage and Administration Instructions

- This is a premixed formulation. Do not dilute prior to use.
- Discard any unused portion of EMERPHED.
- Inspect parenteral drug products visually for particulate matter and discoloration prior to administration, whenever solution and container permit.
- The single-dose prefilled syringe is intended for use in one patient during one surgical procedure.

EMERPHED is a clear, colorless solution. Do not use if the solution is not clear or if particulate matter is present.

2.2 Dosing for the Treatment of Clinically Important Hypotension in the Setting of Anesthesia

The recommended dosages for the treatment of clinically important hypotension in the setting of anesthesia is an initial dose of 5 mg to 10 mg administered by intravenous bolus. Administer additional boluses as needed, not to exceed a total dosage of 50 mg.

- Adjust dosage according to the blood pressure goal (i.e., titrate to effect).

2.3 Instructions for Use of Prefilled Syringe

The proper method of administration of EMERPHED-PFS injection is described in the following instructions.

For each single-dose prefilled syringe:

1. Remove syringe from tray and check that it is not damaged or leaking.
2. Inspect drug product in glass syringe for any visible particulate matter or discoloration prior to use. Discard if particulate matter or discoloration is present.
3. Do not remove the tamper evident seal. Push plunger rod slightly in to break the stopper loose while tip cap is still on.
4. Hold the syringe upright on the syringe barrel (C). With the other hand, take hold of the cap (A) and twist off cap counterclockwise from syringe tip (see Figure 1).
5. Once cap (A) is off, DO NOT TOUCH THE STERILE SYRINGE TIP (Luer-Lok) (B) (see Figure 2).
6. Discard the tip cap.
7. Expel air bubble.
8. Adjust dose into sterile material (if applicable).
9. Connect the syringe to an appropriate intravenous connection.
  - Before injection, ensure that the syringe is securely attached to the needle or needleless luer access device (NLAD).
10. Depress plunger rod to deliver medication. Ensure that pressure is maintained on the plunger rod during the entire administration.
11. Remove syringe from NLAD (if applicable) and discard into appropriate receptacle.
  - To prevent needle stick injuries, do not recap needle when needle is connected to syringe.
  NOTE: All steps must be done sequentially
  - Do not re-sterilize syringe
  - Do not use this product on a sterile field
  - Do not introduce any other fluid into the syringe at any time
  - This product is for single dose only

3. DOSAGE FORMS AND STRENGTHS

EMERPHED (ephedrine sulfate injection) is a clear, colorless solution available as:

- A single-dose vial that contains 50 mg/10 mL (5 mg/mL) ephedrine sulfate, equivalent to 38 mg/10 mL (3.8 mg/mL) ephedrine base.

EMERPHED-PFS (ephedrine sulfate injection) is a clear, colorless solution available as:

- A single-dose 5 mL prefilled syringe that contains 25 mg/5 mL (5 mg/mL) ephedrine sulfate, equivalent to 19 mg/5 mL (3.8 mg/mL) ephedrine base.
- A single-dose pre-filled syringe that contains 50 mg/10 mL (5 mg/mL) ephedrine sulfate, equivalent to 38 mg/10 mL (3.8 mg/mL) ephedrine base.

4. CONTRAINDICATIONS

None

5. WARNINGS AND PRECAUTIONS

5.1 Pressor Effect with Concomitant Oxytocic Drugs

Serious postpartum hypertension has been described in patients who received both a vasopressor (i.e., methoxamine, phenylephrine, ephedrine) and an oxytocic (i.e., methylergonovine, ergonovine) [see Drug Interactions (7)]. Some of these patients experienced a stroke. Carefully monitor the blood pressure of individuals who have received both EMERPHED and EMERPHED-PFS and an oxytocic.

5.2 Tolerance and Tachyphylaxis

Data indicate that repeated administration of ephedrine can result in tachyphylaxis. Be aware of this possibility when treating anesthesia-induced hypotension with EMERPHED and EMERPHED-PFS and be prepared with an alternative pressor to mitigate unacceptable responsiveness.

5.3 Risk of Hypertension When Used Prophylactically

When used to prevent hypotension, ephedrine has been associated with an increased incidence of hypertension compared with when ephedrine is used to treat hypotension.

6. ADVERSE REACTIONS

The following adverse reactions associated with the use of ephedrine sulfate were identified in the literature. Because these reactions are reported voluntarily from a population of uncertain size, it is not always possible to estimate their frequency reliably or to establish a causal relationship to drug exposure.

Gastrointestinal disorders: Nausea, vomiting

Cardiac disorders: Tachycardia, palpitations (thumping heart), reactive hypertension, bradycardia, ventricular ectopics, R-R variability

Nervous system disorders: Dizziness

Psychiatric disorders: Restlessness

7. DRUG INTERACTIONS

Interactions that Augment the Pressor Effect
Oxytocin and oxytocic drugs
Clinical Impact: | Serious postpartum hypertension has been described in patients who received both a vasopressor (i.e., methoxamine, phenylephrine, ephedrine) and an oxytocic (i.e., methylergonovine, ergonovine). Some of these patients experienced a stroke.
Intervention: | Carefully monitor the blood pressure of individuals who have received both EMERPHED and EMERPHED-PFS and an oxytocic.
Clonidine, propofol, monoamine oxidase inhibitors (MAOIs), atropine
Clinical Impact: | These drugs augment the pressor effect of ephedrine.
Intervention: | Carefully monitor the blood pressure of individuals who have received both EMERPHED and EMERPHED-PFS and any of these drugs.
Drugs that Antagonize the Pressor Effect
α-adrenergic antagonists, β-adrenergic receptor antagonists, reserpine, quinidine, mephentermine
Clinical Impact: | These drugs antagonize the pressor effect of ephedrine.
Intervention: | Carefully monitor the blood pressure of individuals who have received both EMERPHED and EMERPHED-PFS and any of these drugs.
Other Drug Interactions
Guanethidine
Clinical Impact: | EMERPHED and EMERPHED-PFS may inhibit the neuron blockage produced by guanethidine, resulting in loss of antihypertensive effectiveness.
Intervention: | Clinician should monitor patient for blood pressor response and adjust the dosage or choice of pressor accordingly.
Rocuronium
Clinical Impact: | EMERPHED and EMERPHED-PFS may reduce the onset time of neuromuscular blockade when used for intubation with rocuronium if administered simultaneously with anesthetic induction.
Intervention: | Be aware of this potential interaction. No treatment or other interventions are needed.
Epidural anesthesia
Clinical Impact: | EMERPHED and EMERPHED-PFS may decrease the efficacy of epidural blockade by hastening the regression of sensory analgesia.
Intervention: | Monitor and treat the patient according to clinical practice.
Theophylline
Clinical Impact: | Concomitant use of EMERPHED and EMERPHED-PFS may increase the frequency of nausea, nervousness, and insomnia.
Intervention: | Monitor patient for worsening symptoms and manage symptoms according to clinical practice.
Cardiac glycosides
Clinical Impact: | Giving EMERPHED and EMERPHED-PFS with a cardiac glycoside, such as digitalis, may increase the possibility of arrhythmias.
Intervention: | Carefully monitor patients on cardiac glycosides who are also administered ephedrine.

8. USE IN SPECIFIC POPULATIONS

8.1 Pregnancy

Risk Summary

Available data from randomized studies, case series, and reports of ephedrine sulfate use in pregnant women have not identified a drug-associated risk of major birth defects, miscarriage, or adverse maternal or fetal outcomes. However, there are clinical considerations due to underlying conditions [see Clinical Considerations]. In animal reproduction studies, decreased fetal survival and fetal body weights were observed in the presence of maternal toxicity after normotensive pregnant rats were administered 60 mg/kg intravenous ephedrine sulfate (12 times the maximum recommended human dose (MRHD) of 50 mg/day). No malformations or embryofetal adverse effects were observed when pregnant rats or rabbits were treated with intravenous bolus doses of ephedrine sulfate during organogenesis at doses 1.9 and 7.7 times the MRHD, respectively [See data].

The estimated background risk of major birth defects and miscarriage for the indicated population is unknown. All pregnancies have a background risk of birth defect, loss, or other adverse outcomes. In the U.S. general population, the estimated background risk of major birth defects and miscarriage in clinically recognized pregnancies is 2 to 4% and 15 to 20%, respectively.

Clinical Considerations

Disease-associated maternal and/or embryofetal risk

Untreated hypotension associated with spinal anesthesia for cesarean section is associated with an increase in maternal nausea and vomiting. A decrease in uterine blood flow due to maternal hypotension may result in fetal bradycardia and acidosis.

Fetal/Neonatal Adverse Reactions

Cases of potential metabolic acidosis in newborns at delivery with maternal ephedrine exposure have been reported in the literature. These reports describe umbilical artery pH of ≤7.2 at the time of delivery [see Clinical Pharmacology 12.3]. Monitoring of the newborn for signs and symptoms of metabolic acidosis may be required. Monitoring of infant's acid-base status is warranted to ensure that an episode of acidosis is acute and reversible.

Data

Animal Data

Decreased fetal body weights were observed when pregnant rats were administered intravenous bolus doses of 60 mg/kg ephedrine sulfate (12 times the maximum recommended human dose (MRHD) of 50 mg based on body surface area) from Gestation Day 6-17. This dose was associated with evidence of maternal toxicity (decreased body weight of dams and abnormal head movements). No malformations or fetal deaths were noted at this dose. No effects on fetal body weight were noted at 10 mg/kg (1.9 times the MRHD of 50 mg).

No evidence of malformations or embryo-fetal toxicity were noted in pregnant rabbits administered intravenous bolus doses up to 20 mg/kg ephedrine sulfate (7.7 times the maximum recommended human dose (MRHD) of 50 mg based on body surface area) from Gestation Day 6-20. This dose was associated with expected pharmacological maternal effects (increased respiration rate, dilated pupils, piloerection).

Decreased fetal survival and body weights in the presence of maternal toxicity (increased mortality) were noted when pregnant dams were administered intravenous bolus doses of 60 mg/kg epinephrine sulfate (approximately 12 times the MRHD based on body surface area) from GD 6 through Lactation Day 20. No adverse effects were noted at 10 mg/kg (1.9 times the MRHD).

8.2 Lactation

Risk Summary

A single published case report indicates that ephedrine is present in human milk. However, no information is available on the effects of the drug on the breastfed infant or the effects of the drug on milk production. The developmental and health benefits of breastfeeding should be considered along with the mother's clinical need for EMERPHED or EMERPHED-PFS and any potential adverse effects on the breastfed child from EMERPHED and EMERPHED-PFS or from the underlying maternal condition.

8.4 Pediatric Use

Safety and effectiveness of EMERPHED and EMERPHED-PFS in pediatric patients have not been established.

Animal Toxicity Data

In a study in which juvenile rats were administered intravenous bolus doses of 2, 10, or 60 mg/kg ephedrine sulfate daily from Postnatal Day 35 to 56, an increased incidence of mortality was noted at the high dose of 60 mg/kg. The no-adverse-effect level was 10 mg/kg (approximately 1.9 times a maximum daily dose of 50 mg in a 60 kg person based on body surface area)

8.5 Geriatric Use

Clinical studies of ephedrine did not include sufficient numbers of subjects aged 65 and over to determine whether they respond differently from younger subjects. Other reported clinical experience has not identified differences in responses between the elderly and younger patients. In general, dose selection for an elderly patient should be cautious, usually starting at the low end of the dosing range, reflecting the greater frequency of decreased hepatic, renal, or cardiac function, and of concomitant disease or other drug therapy.

This drug is known to be substantially excreted by the kidney, and the risk of adverse reactions to this drug may be greater in patients with impaired renal function. Because elderly patients are more likely to have decreased renal function, care should be taken in dose selection, and it may be useful to monitor renal function.

8.6 Renal Impairment

Ephedrine and its metabolite are excreted in urine. In patients with renal impairment, excretion of ephedrine is likely to be affected with a corresponding increase in elimination half-life, which will lead to slow elimination of ephedrine and consequently prolonged pharmacological effect and potentially adverse reactions. Monitor patients with renal impairment carefully after the initial bolus dose for adverse events.

10. OVERDOSAGE

Overdose of EMERPHED and EMERPHED-PFS can cause a rapid rise in blood pressure. In the case of an overdose, careful monitoring of blood pressure is recommended. If blood pressure continues to rise to an unacceptable level, parenteral antihypertensive agents can be administered at the discretion of the clinician.

11. DESCRIPTION

EMERPHED / EMERPHED-PFS (ephedrine sulfate injection) is a clear, colorless, sterile solution for intravenous injection. The chemical name of ephedrine sulfate is benzenemethanol, α-[1-(methylamino)ethyl]-, [R-(R*,S*)]-, sulfate (2:1) (salt), and the molecular weight is 428.5 g/mol. Its structural formula is depicted below:

Ephedrine sulfate is freely soluble in water and ethanol, very slightly soluble in chloroform, and practically insoluble in ether. Each mL contains ephedrine sulfate, USP 5 mg (equivalent to 3.8 mg ephedrine base), 0.9% sodium chloride, USP in water for injection. The pH range is 4.5 to 7.0.

12. CLINICAL PHARMACOLOGY

12.1 Mechanism of Action

Ephedrine sulfate is a sympathomimetic amine that directly acts as an agonist at α- and β-adrenergic receptors and indirectly causes the release of norepinephrine from sympathetic neurons. Pressor effects by direct alpha- and beta-adrenergic receptor activation are mediated by increases in arterial pressures, cardiac output, and peripheral resistance. Indirect adrenergic stimulation is caused by norepinephrine release from sympathetic nerves.

12.2 Pharmacodynamics

Ephedrine stimulates heart rate and cardiac output and variably increases peripheral resistance; as a result, ephedrine usually increases blood pressure. Stimulation of the α-adrenergic receptors of smooth muscle cells in the bladder base may increase the resistance to the outflow of urine. Activation of β- adrenergic receptors in the lungs promotes bronchodilation.

The overall cardiovascular effect from ephedrine is the result of a balance among α-1 adrenoceptor- mediated vasoconstriction, β-2 adrenoceptor- mediated vasoconstriction, and β-2 adrenoceptor-mediated vasodilatation. Stimulation of the β-1 adrenoceptors results in positive inotrope and chronotrope action.

Tachyphylaxis to the pressor effects of ephedrine may occur with repeated administration [see Warnings and Precautions 5.2].

12.3 Pharmacokinetics

Publications studying pharmacokinetics of oral administration of (-)-ephedrine support that (-)-ephedrine is metabolized into norephedrine. However, the metabolism pathway is unknown. Both the parent drug and the metabolite are excreted in urine. Limited data after IV administration of ephedrine support similar observations of urinary excretion of drug and metabolite. The plasma elimination half-life of ephedrine following oral administration was about 6 hours.

Ephedrine crosses the placental barrier [see Use in Specific Populations 8.1].

13. NONCLINICAL TOXICOLOGY

13.1 Carcinogenesis, Mutagenesis, Impairment of Fertility

Carcinogenesis: Two-year feeding studies in rats and mice conducted under the National Toxicology Program (NTP) demonstrated no evidence of carcinogenic potential with ephedrine sulfate at doses up to 10 mg/kg/day and 27 mg/kg/day (approximately 2 times and 3 times the maximum human recommended dose on a mg/m2 basis, respectively).

Mutagenesis: Ephedrine sulfate tested negative in the in vitro bacterial reverse mutation assay, the in vitro mouse lymphoma assay, the in vitro sister chromatid exchange, the in vitro chromosomal aberration assay, and the in vivo rat bone marrow micronucleus assay.

Impairment of Fertility: There was no impact on fertility or early embryonic development in a study in which male rats were administered intravenous bolus doses of 0, 2, 10, or 60 mg/kg ephedrine sulfate (up to 12 times the maximum recommended human dose of 50 mg based on body surface area) for 28 days prior to mating and through gestation and females were treated for 14 days prior to mating through Gestation Day 7.

14. CLINICAL STUDIES

The evidence for the efficacy of EMERPHED / EMERPHED-PFS (ephedrine sulfate injection) is derived from the published literature. Increases in blood pressure following administration of ephedrine were observed in 14 studies, including 9 where ephedrine was used in pregnant women undergoing neuraxial anesthesia during Cesarean delivery, 1 study in non-obstetric surgery under neuraxial anesthesia, and 4 studies in patients undergoing surgery under general anesthesia. Ephedrine has been shown to raise systolic and mean blood pressure when administered as a bolus dose following the development of hypotension during anesthesia.

16. HOW SUPPLIED/STORAGE AND HANDLING

EMERPHED (ephedrine sulfate injection) is a clear, colorless solution available as single-dose vials containing 5 mg/mL ephedrine sulfate, equivalent to 3.8 mg/mL ephedrine base and is supplied as follows:

NDC | Presentation
14789-250-07 | 10 mL clear glass, single-dose vial; strength 50 mg/10 mL (5 mg/mL)
14789-250-10 | 10 mL vials packaged in a carton of 10

EMERPHED-PFS (ephedrine sulfate injection) is a clear, colorless solution available as single-dose pre-filled syringes containing 5 mg/mL ephedrine sulfate, equivalent to 3.8 mg/mL ephedrine base and is supplied as follows:

NDC | Presentation
14789-251-09 | 5 mL clear glass, single-dose pre-filled syringe; strength 25 mg/5 mL (5 mg/mL)
14789-251-10 | 5 mL pre-filled syringes packaged in a carton of 10
14789-252-09 | 10 mL clear glass, single-dose pre-filled syringe; strength 50 mg/10 mL (5 mg/mL)
14789-252-10 | 10 mL pre-filled syringes packaged in a carton of 10

The single-dose prefilled syringes, each fitted with a removable tip cap and plunger rods, are presented in a carton.

EMERPHED (ephedrine sulfate injection) 50 mg/10 mL (5 mg/mL) and EMERPHED-PFS (ephedrine sulfate injection) 50 mg/10 mL (5 mg/mL) and 25 mg/5 mL (5 mg/mL) are not made with natural rubber latex.

Store at 25°C (77°F); excursions permitted to 15°C to 30°C (59°F to 86°F) [see USP Controlled Room Temperature].

Store in carton until time of use. For single dose only. Discard unused portion.

The single-dose prefilled syringe is intended for use in one patient during one surgical procedure.

Patent, www.emerphed.com/patent

Manufactured in Italy for:

Nexus Pharmaceuticals, LLC

400 Knightsbridge Parkway

Lincolnshire, IL 60069

USA

EPFPI01ITR06

Principal Display Panel – 5 mg/mL Carton Label

NDC 14789-252-10

Rx Only

EMERPHED®-PFS

(ephedrine sulfate injection)

50 mg/10 mL (5 mg/mL)
(equivalent to 38 mg/10 mL ephedrine base)

Premixed formulation -Do not dilute

For Intravenous Use Only

10 x 10 mL Single-dose Prefilled Syringes

NEXUS
PHARMACEUTICALS

Principal Display Panel – 5 mg/mL Vial Label

NDC 14789-252-09

Rx Only

EMERPHED®-EPF

(ephedrine sulfate injection)

50 mg/10 mL (5 mg/mL)
(equivalent to 38 mg/5 mL ephedrine base)

Premixed formulation –Do not dilute

For Intravenous Use Only

10 mL Single-dose Prefilled Syringe

PACKAGE LABEL

Principal Display Panel – 25 mg/5 mL Carton Label

NDC 14789-251-10

Rx Only

EMERPHED®-EPF

(ephedrine sulfate injection)

25 mg/5 mL (5 mg/mL)
(equivalent to 19 mg/5 mL ephedrine base)

Premixed formulation -Do not dilute

For Intravenous Use Only

10 x 5 mL Single-dose Prefilled Syringes

NEXUS
PHARMACEUTICALS

PACKAGE LABEL

Principal Display Panel – 25 mg/5 mL Vial Label

NDC 14789-251-09

Rx Only

EMERPHED®-EPF

(ephedrine sulfate injection)

25 mg/5 mL (5 mg/mL)
(equivalent to 19 mg/5 mL ephedrine base)

Premixed formulation –Do not dilute

For Intravenous Use Only

5 mL Single-dose Prefilled Syringe